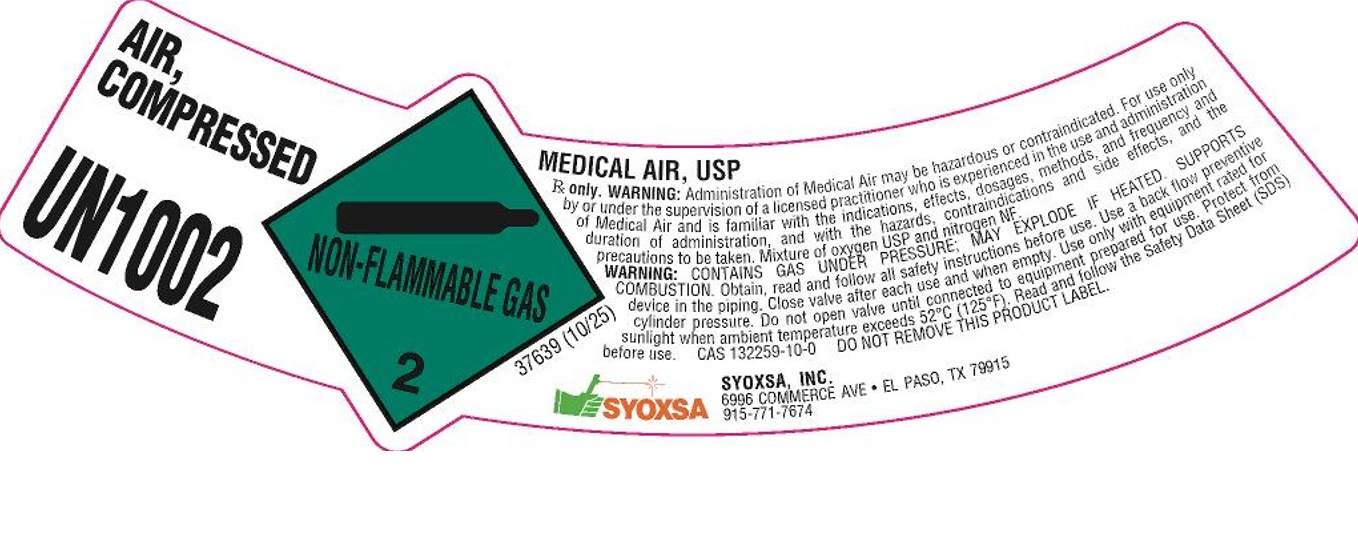 DRUG LABEL: Air
NDC: 23647-003 | Form: GAS
Manufacturer: SYOXSA, Inc.
Category: prescription | Type: HUMAN PRESCRIPTION DRUG LABEL
Date: 20251212

ACTIVE INGREDIENTS: OXYGEN 210 mL/1 L

Air

PACKAGE LABEL

AIR, COMPRESSED

UN1002

MEDICAL AIR, USP

Rx only. WARNING: Administration of Medical Air may be hazardous or contraindicated. For use only by or under the supervision of a licensed practitioner who is experienced in the use and administration of Medical Air and is familiar with the indications, effects, dosages, methods, and frequency and duration of administration, and with the hazards, contraindications and side effects, and the precautions to be taken. Mixture of oxygen USP and nitrogen NF.

WARNING: CONTAINS GAS UNDER PRESSURE; MAY EXPLODE IF HEATED. SUPPORTS COMBUSTION. Obtain, read and follow all safety instructions before use. Use a back flow preventive device in the piping. Close valve after each use and when empty. Use only with equipment rated for cylinder pressure. Do not open valve until connected to equipment prepared for use. Protect from sunlight when ambient temperature exceeds 52 C (125 F). Read and follow the Safety Data Sheet (SDS) before use. CAS 132259-10-0 DO NOT REMOVE THIS PRODUCT LABEL.

SYOXSA

SYOXSA, INC.

6996 COMMERCE AVE EL PASSO, TX 79915

915-771-7674